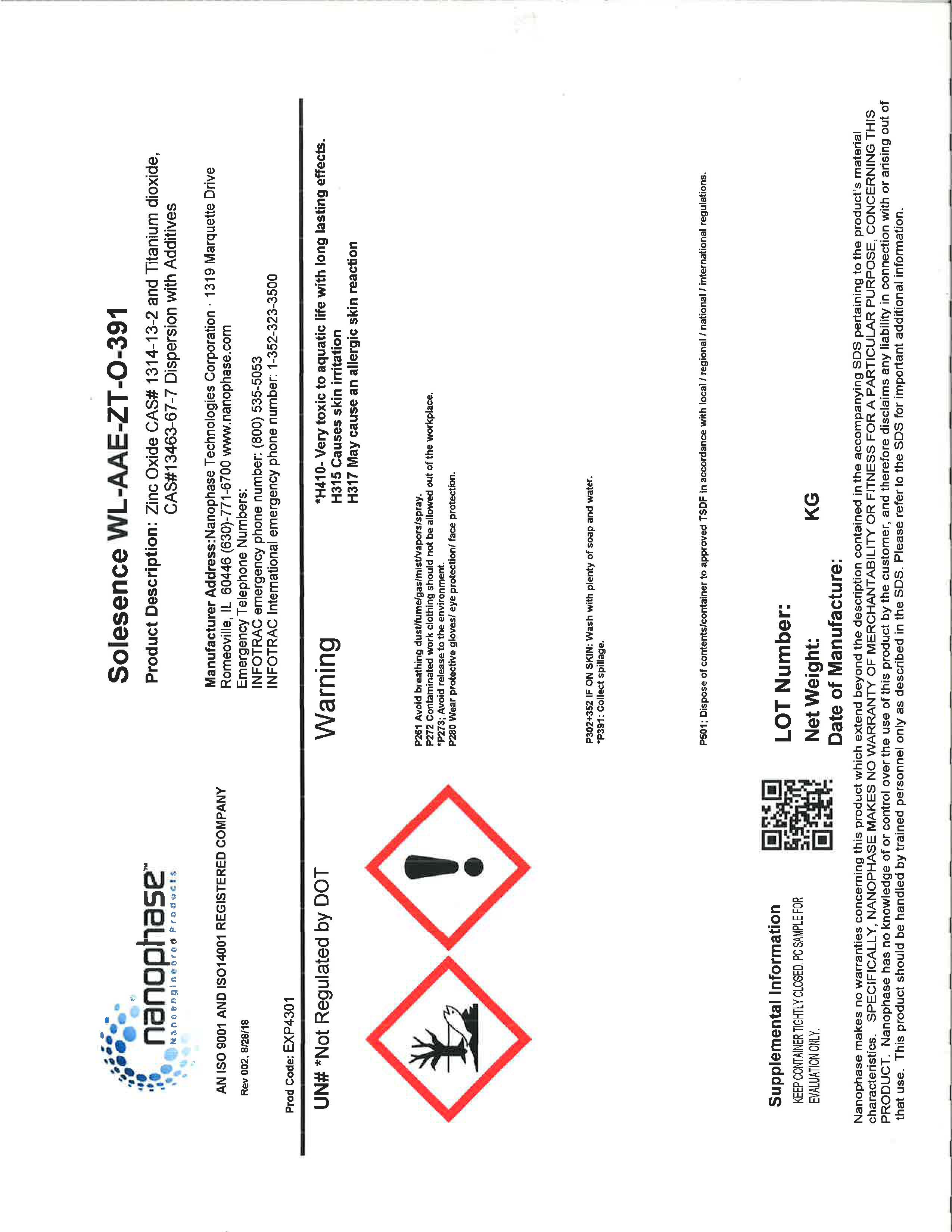 DRUG LABEL: WL-AAE-ZT-O-391
NDC: 63931-4301 | Form: LOTION
Manufacturer: Nanophase Technologies Corporation
Category: otc | Type: HUMAN OTC DRUG LABEL
Date: 20220117

ACTIVE INGREDIENTS: ZINC OXIDE 1 g/1 g; TITANIUM DIOXIDE 1 g/1 g
INACTIVE INGREDIENTS: DIMETHICONOL/PROPYLSILSESQUIOXANE/SILICATE CROSSPOLYMER (450000000 MW) 1 g/1 g

WL-AAE-ZT-O-391 (Bulk for PROTECT DAILY CREAM SPF 40)